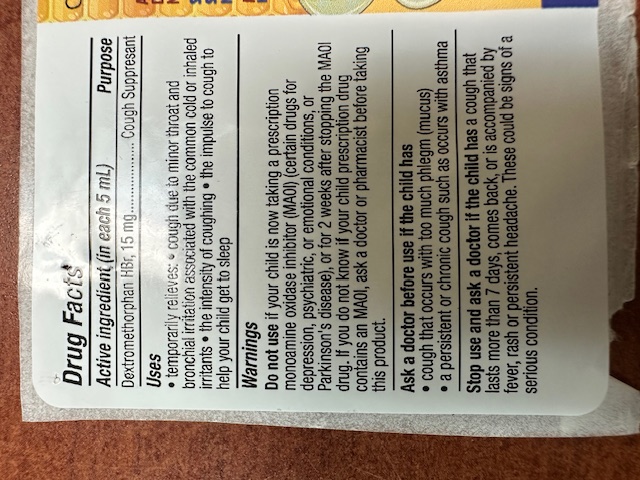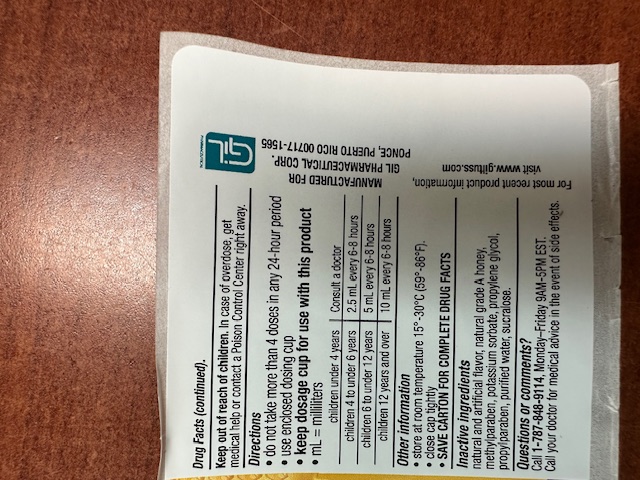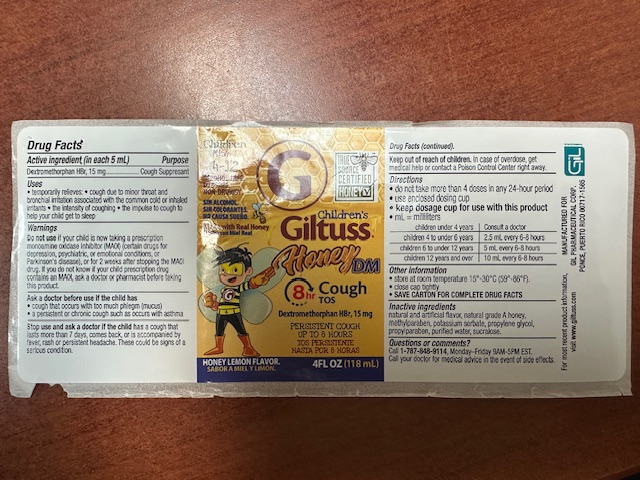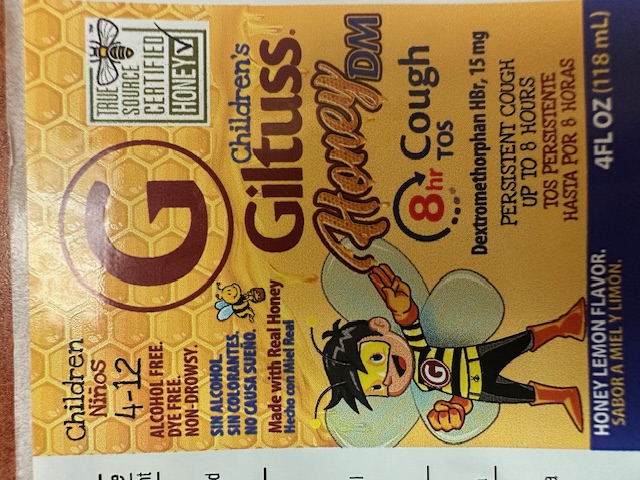 DRUG LABEL: Childrens Giltuss Honey DM Cough
NDC: 65852-007 | Form: LIQUID
Manufacturer: Dextrum Laboratories Inc
Category: otc | Type: HUMAN OTC DRUG LABEL
Date: 20250917

ACTIVE INGREDIENTS: DEXTROMETHORPHAN HYDROBROMIDE 15 mg/5 mL
INACTIVE INGREDIENTS: POTASSIUM SORBATE; HONEY; METHYLPARABEN; PROPYLPARABEN; WATER; PROPYLENE GLYCOL; SUCRALOSE

Giltuss Honey DM

KEEP OUT OF REACH OF CHILDREN

in case of overdose, get medical help or contact a Poison Control Center right away

INDICATIONS AND USAGE

Do not take more than 4 doses in any 24 hours period Keep sosage cup for use with this product

children under 4 years, consult a doctor

children 6 to under 12 years, 5ml every 6-8 hours

children 12 years and over, 10ml every 6-8 hours

Active ingredient (in each 5ml)

Active Ingredients (in each 5 mL)

Dextromethorphan15mg

purpose cough suppresant

Do not use if your child is taking a prescription monoamine oxidase inhibitor (MAOI) (certain drugs fotdepression, psychriatic or emotional condition, orParkinso's desese), or for 2 weeksafter stoppings the MAOI drugs. If you do not know if your child prescription drug contains an MAOI, ask a doctor or pharmacist before taking this product.

Stop use and ask a doctorif the child has a cough that last more than 7 days, comes back or is accompanied byfever, rash or persistent headache. These could be signs of a serius condition.

Purpose section Cough Suppresant

Ask a doctor before use if the child has couhg that occurs with too muchmucus

a persistent or chronic cough such as occurs with sthma.

OTHER SAFETY INFORMATION

Temporarily relieves: cough due to minor thoroat and brochial irritation associated with the common cold or inhaled irritants

the intensity of coughing

The impulse to cough to help your child get to sleep

QUESTIONS

Call 1-787-848-9114 Monday-Friday, 9AM-5PM EST

Call your doctor for medeical advice in the event of side effects.

Dosage and administration

Do not take more than 4 doses in any 24 hours period Keep sosage cup for use with this product

children under 4 years, consult a doctor

children 6 to under 12 years, 5ml every 6-8 hours

children 12 years and over, 10ml every 6-8 hours

Inactive ingredient

Inactive ingredients:

Natural and artificial flavor, natural grade A Honey, Methylparaben, potassium Sorbate, propylene Glycol, propylparaben, purified water, sucralose

Principal display panel

Children giltuss honey DM 4-12

Alcohol Free

DYE free

Non Drowsy

Certified Honey

Honey Lemon Flavor